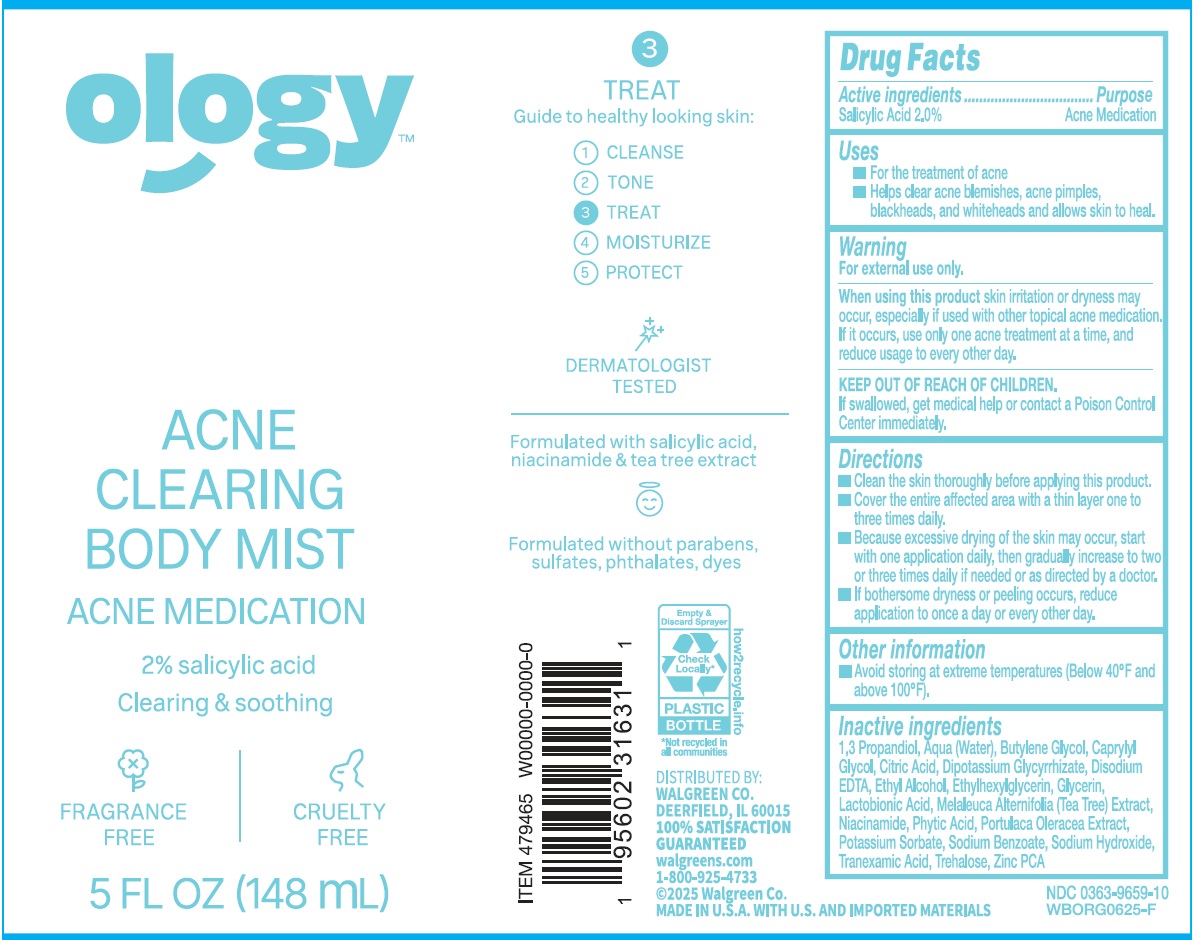 DRUG LABEL: Ology Acne Clearing Body Mist
NDC: 0363-9659 | Form: GEL
Manufacturer: Walgreens Co.
Category: otc | Type: HUMAN OTC DRUG LABEL
Date: 20250812

ACTIVE INGREDIENTS: SALICYLIC ACID 20 mg/1 mL
INACTIVE INGREDIENTS: PROPANEDIOL; WATER; BUTYLENE GLYCOL; CAPRYLYL GLYCOL; CITRIC ACID; GLYCYRRHIZINATE DIPOTASSIUM; EDETATE DISODIUM; ALCOHOL; ETHYLHEXYLGLYCERIN; GLYCERIN; LACTOBIONIC ACID; MELALEUCA ALTERNIFOLIA LEAF; NIACINAMIDE; PHYTIC ACID; PURSLANE; POTASSIUM SORBATE; SODIUM BENZOATE; SODIUM HYDROXIDE; TRANEXAMIC ACID; TREHALOSE; ZINC PIDOLATE

Ology Acne Clearing Body Mist

Active ingredients

Salicylic Acid 2.0%

Purpose

Acne Medication

Uses

- For the treatment of acne
- Helps clear acne blemishes, acne pimples, blackheads, and whiteheads and allows skin to heal.

Warning

For external use only.

When using this product

skin irritation or dryness may occur, especially if used with other topical acne medication. If it occurs, use only one ance treatment at a time, and reduce usage to every other day.

KEEP OUT OF REACH OF CHILDREN.

If swallowed, get medical help or contact a Poison Control Center immediately.

Directions

- Clean the skin thoroughly before applying this product.
- Cover the entire affected area with a thin layer one to three times daily.
- Because excessive drying of the skin may occur, start with one application daily, then gradually increase to two or three times daily if needed or as directed by a doctor.
- If bothersome dryness or peeling occurs, reduce application to once a day or every other day.

Other information

- Avoid storing at extreme temperatures (Below 40ºF and above 100ºF).

Inactive ingredients

1,3 Propanediol, Aqua (Water), Butylene Glycol, Caprylyl Glycol, Citric Acid, Dipotassium Glycyrrhizate, Disodium EDTA, Ethyl Alcohol, Ethylhexylglycerin, Glycerin, Lactobionic Acid, Melaleuca Alternifolia (Tea Tree) Extract, Niacinamide, Phytic Acid, Portulaca Oleracea Extract, Potassium Sorbate, Sodium Benzoate, Sodium Hydroxide, Tranexamic Acid, Trehalose, Zinc PCA